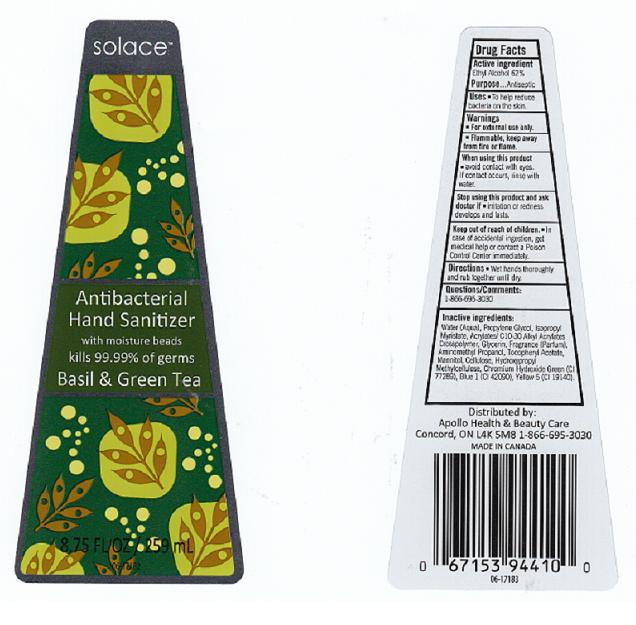 DRUG LABEL: ANTIBACTERIAL HAND SANITIZER
NDC: 63148-269 | Form: GEL
Manufacturer: APOLLO HEALTH AND BEAUTY CARE
Category: otc | Type: HUMAN OTC DRUG LABEL
Date: 20110412

ACTIVE INGREDIENTS: ALCOHOL 62 mL/100 mL
INACTIVE INGREDIENTS: WATER; PROPYLENE GLYCOL; ISOPROPYL MYRISTATE; CARBOMER COPOLYMER TYPE A; GLYCERIN; AMINOMETHYLPROPANOL; .ALPHA.-TOCOPHEROL ACETATE, D-; MANNITOL; POWDERED CELLULOSE; HYPROMELLOSES; CHROMIC OXIDE; FD&C BLUE NO. 1; FD&C YELLOW NO. 5

DRUG FACTS

ACTIVE INGREDIENT

ETHYL ALCOHOL 62 PERCENT

PURPOSE

ANTISEPTIC

USES

TO HELP REDUCE BACTERIA ON THE SKIN.

WARNINGS

FOR EXTERNAL USE ONLY.

FLAMMABLE. KEEP AWAY FROM FIRE OR FLAME.

WHEN USING THIS PRODUCT

AVOID CONTACT WITH EYES. IF CONTACT OCCURS, RINSE THROUGHLY WITH WATER.

DIRECTIONS

WET HANDS THOROUGHLY AND RUB TOGETHER UNTIL DRY.

STOP USING THIS PRODUCT AND ASK DOCTOR IF

IRRITATION OR REDNESS DEVELOPS AND LASTS.

KEEP OUT OF REACH OF CHILDREN

IN CASE OF ACCIDENTAL INGESTION, GET MEDICAL HELP OR CONTACT A POISON CONTROL CENTER IMMEDIATELY.

QUESTIONS OR COMMENTS

1-866-695-3030

INACTIVE INGREDIENTS

WATER, PROPYLENE GLYCOL, ISOPROPYL MYRISTATE, ACRYLATES/ C10-30 ALKYL ACRYLATES CROSSPOLYMER, GLYCERIN, FRAGRANCE, AMINOMETHYL PROPANOL, TOCOPHERYL ACETATE, MANNITOL, CELLULOSE, HYDROXYPROPYL METHYLCELLULOSE, CHROMIUM HYDROXIDE GREEN (CI 77289), BLUE 1 (CI 42090), YELLOW 5 (CI 19140).